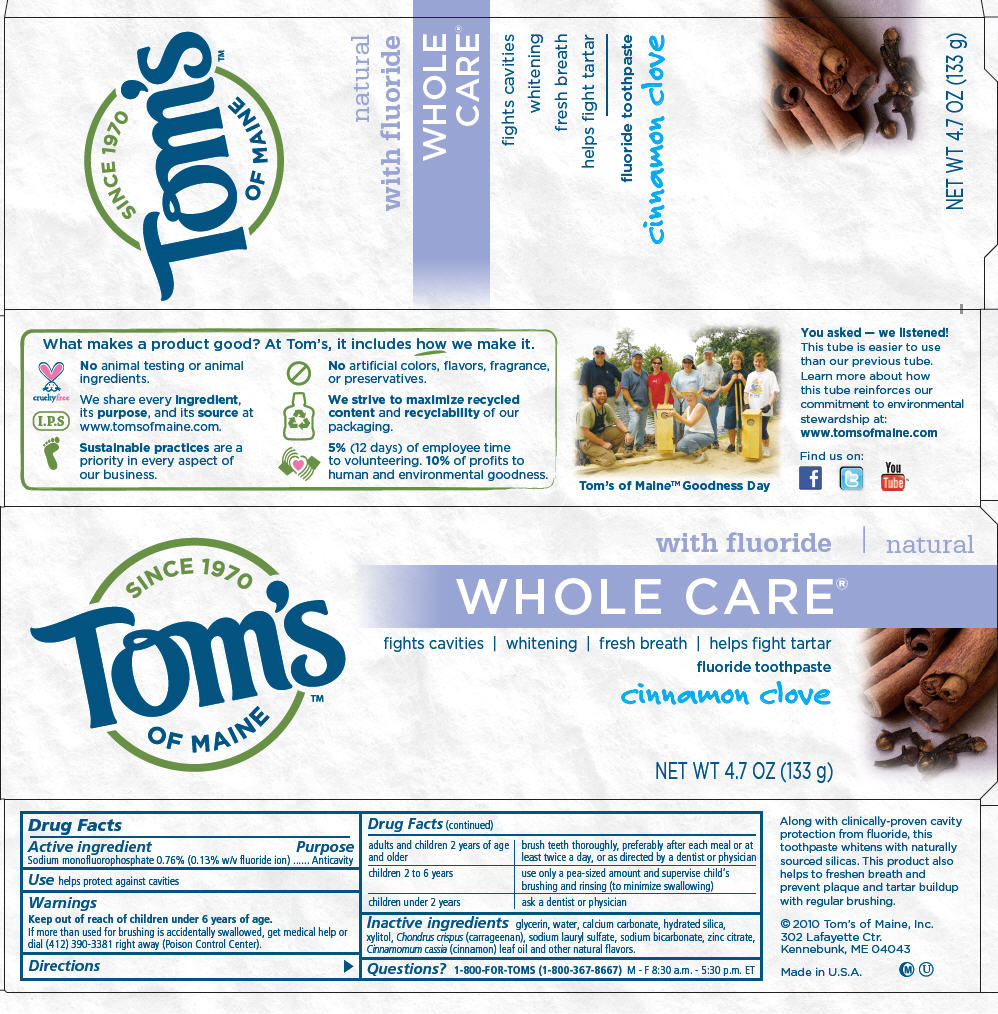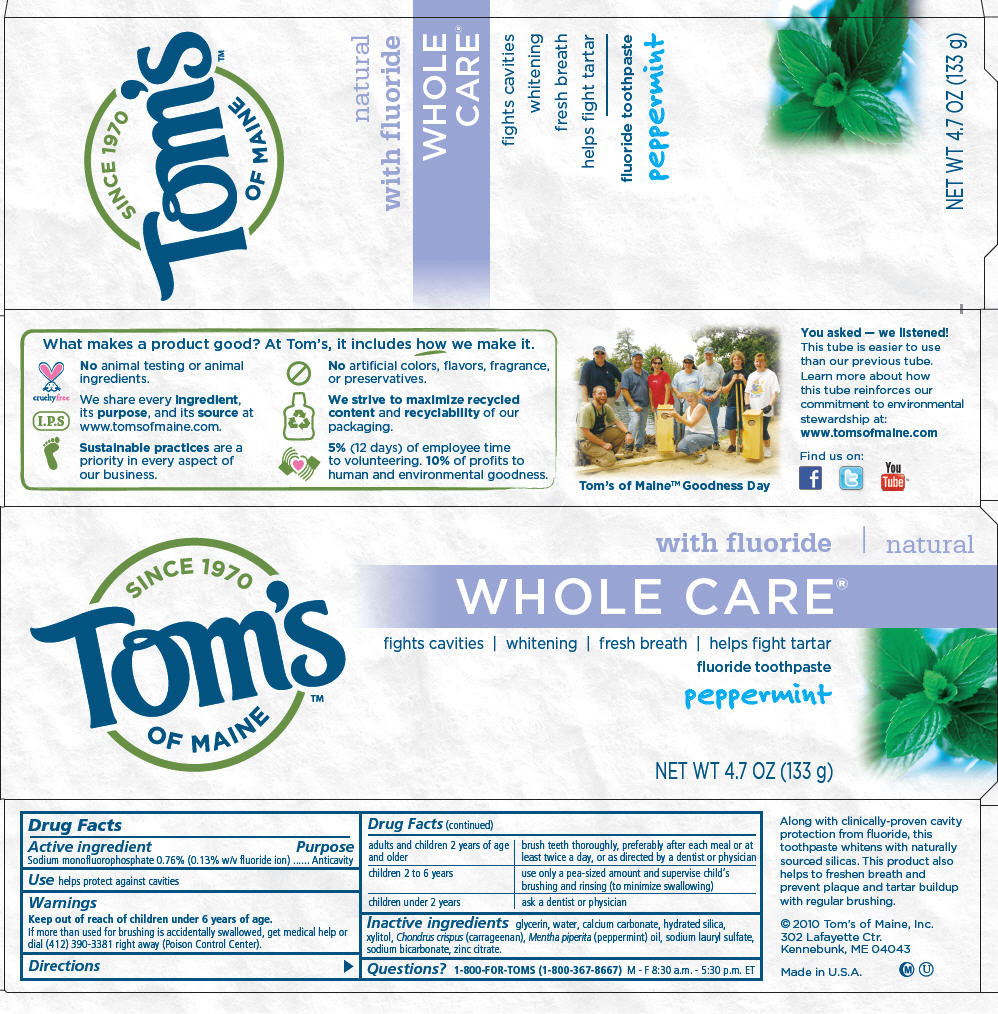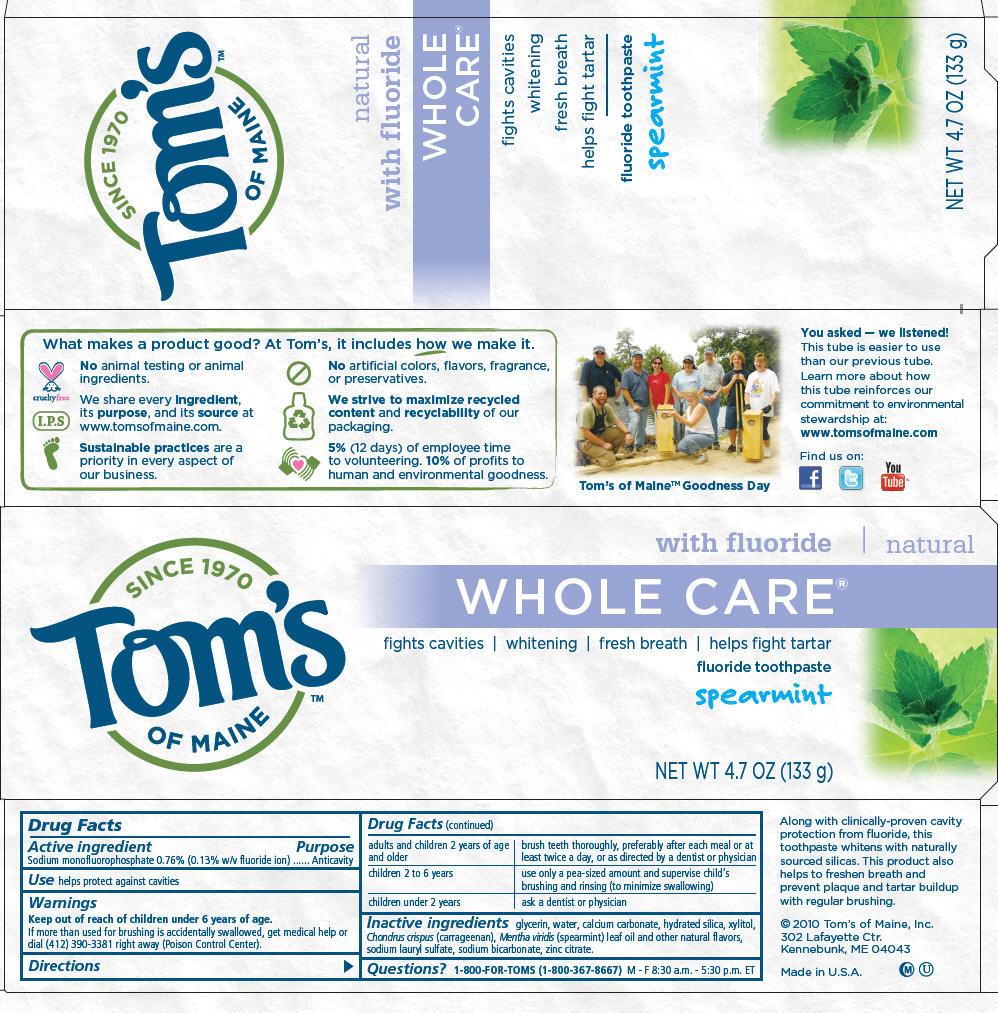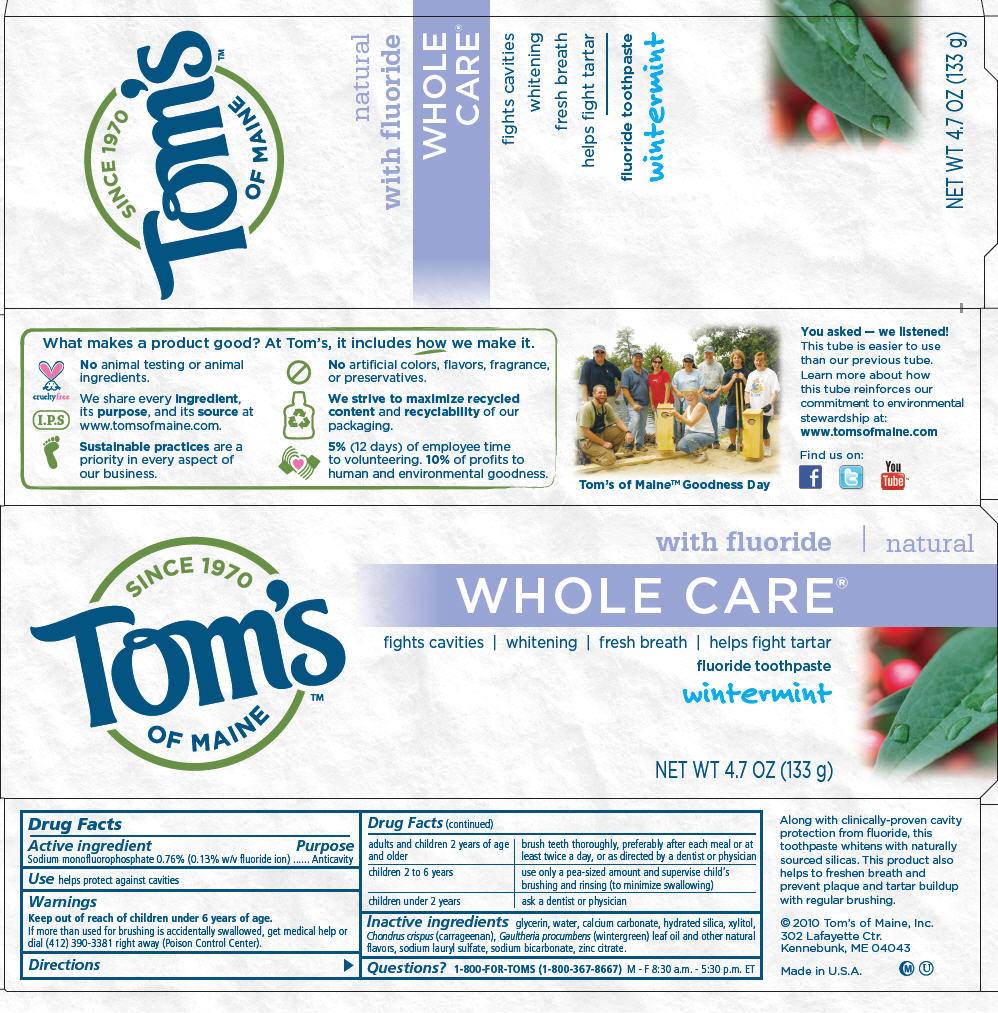 DRUG LABEL: Whole Care 
NDC: 51009-100 | Form: PASTE, DENTIFRICE
Manufacturer: Tom's of Maine, Inc.
Category: otc | Type: HUMAN OTC DRUG LABEL
Date: 20110211

ACTIVE INGREDIENTS: Sodium monofluorophosphate 0.0076 g/1 g
INACTIVE INGREDIENTS: Glycerin; Water; Calcium carbonate; Hydrated Silica; Xylitol; Carrageenan; Zinc citrate; Sodium Lauryl Sulfate; Cinnamon leaf oil; Clove oil; Clove stem oil

Tom's
OF MAINE
WHOLE CARE
fluoride toothpaste

Drug Facts

Active ingredient

Sodium monofluorophosphate 0.76% (0.13% w/v fluoride ion)

Purpose

Anticavity

Use

helps protect against cavities

Warnings

Keep out of reach of children under 6 years of age.

If more than used for brushing is accidentally swallowed, get medical help or dial (412) 390-3381 right away (Poison Control Center).

Directions

adults and children 2 years of age and older | brush teeth thoroughly, preferably after each meal or at least twice a day, or as directed by a dentist or physician
children 2 to 6 years | use only a pea-sized amount and supervise child's brushing and rinsing (to minimize swallowing)
children under 2 years | ask a dentist or physician

Inactive ingredients

glycerin, water, calcium carbonate, hydrated silica, xylitol, Chondrus crispus (carrageenan), sodium lauryl sulfate, sodium bicarbonate, zinc citrate, Cinnamomum cassia (cinnamon) leaf oil and other natural flavors.

Questions?

1-800-FOR-TOMS (1-800-367-8667) M - F 8:30 a.m. - 5:30 p.m. ET

PRINCIPAL DISPLAY PANEL - 133 g Carton

Since 1970
Tom's
OF MAINE™

with fluoride | natural

WHOLE CARE®

fights cavities | whitening | fresh breath | helps fight tartar
fluoride toothpaste

cinnamon clove

NET WT 4.7 OZ (133 g)

PRINCIPAL DISPLAY PANEL - 133 g Carton

Since 1970
Tom's
OF MAINE™

with fluoride | natural

WHOLE CARE®

fights cavities | whitening | fresh breath | helps fight tartar
fluoride toothpaste

peppermint

NET WT 4.7 OZ (133 g)

PRINCIPAL DISPLAY PANEL - 133 g Carton

Since 1970
Tom's
OF MAINE™

with fluoride | natural

WHOLE CARE®

fights cavities | whitening | fresh breath | helps fight tartar
fluoride toothpaste

spearmint

NET WT 4.7 OZ (133 g)

PRINCIPAL DISPLAY PANEL - 133 g Carton

Since 1970
Tom's
OF MAINE™

with fluoride | natural

WHOLE CARE®

fights cavities | whitening | fresh breath | helps fight tartar
fluoride toothpaste

wintermint

NET WT 4.7 OZ (133 g)